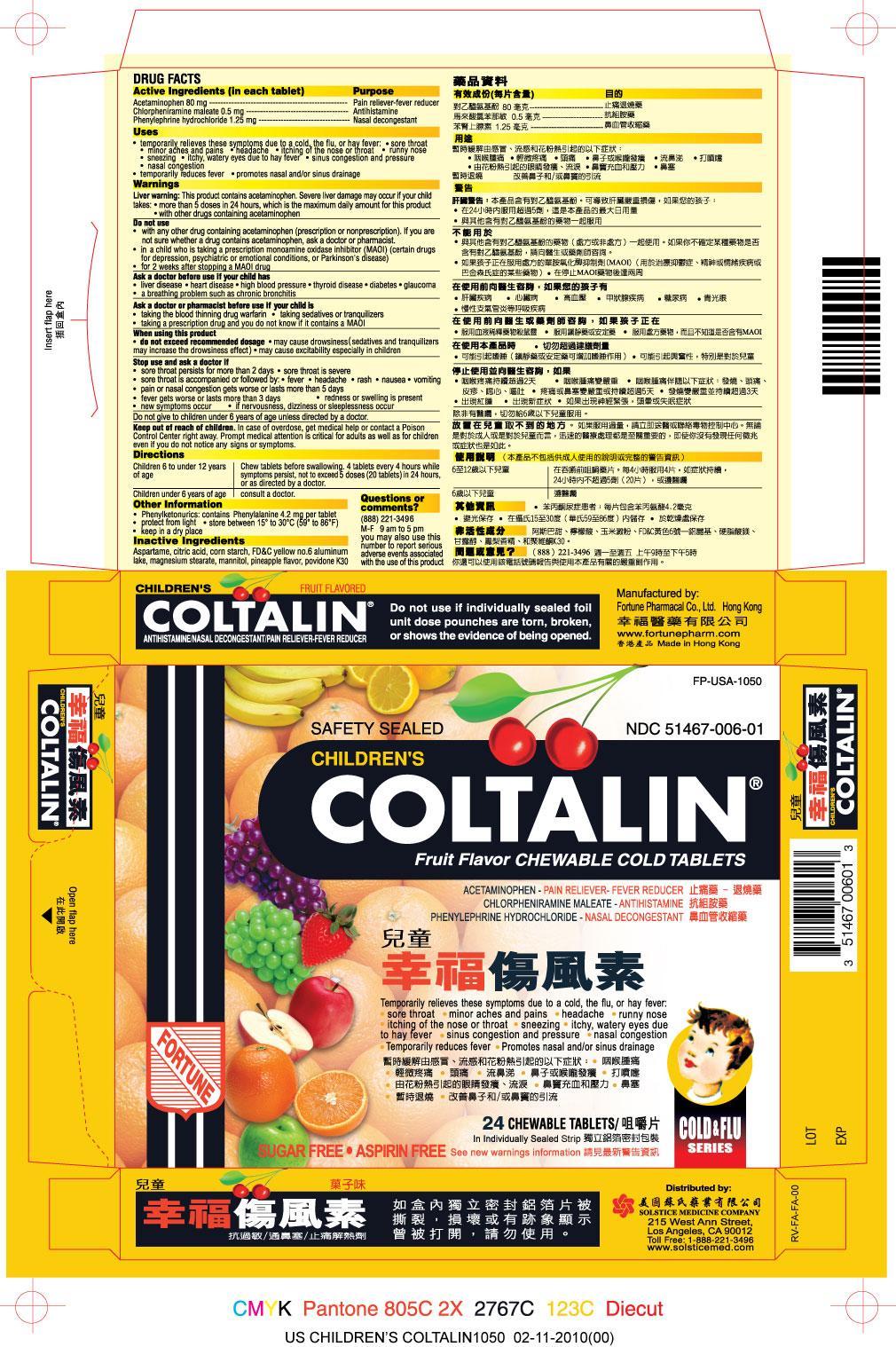 DRUG LABEL: CHILDRENS COLTALIN
NDC: 51467-006 | Form: TABLET, CHEWABLE
Manufacturer: FORTUNE PHARMACAL COMPANY LIMITED
Category: otc | Type: HUMAN OTC DRUG LABEL
Date: 20251113

ACTIVE INGREDIENTS: ACETAMINOPHEN 80 mg/1 1; CHLORPHENIRAMINE MALEATE 0.5 mg/1 1; PHENYLEPHRINE HYDROCHLORIDE 1.25 mg/1 1
INACTIVE INGREDIENTS: ASPARTAME; CITRIC ACID MONOHYDRATE; STARCH, CORN; FD&C YELLOW NO. 6; MAGNESIUM STEARATE; MANNITOL; PINEAPPLE; POVIDONE K30

Drug Facts

Active ingredients (in each tablet)
Acetaminophen 80 mg
Chlorpheniramine maleate 0.5 mg
Phenylephrine hydrochloride 1.25 mg

Purpose
Pain reliever-fever reducer
Antihistamine
Nasal decongestant

Uses
temporarily relieves these symptoms due to a cold, the flu, or hay fever:
sore throat
minor aches and pains
headache
itching of the nose or throat
runny nose
sneezing itchy, watery eyes due to hay fever
sinus congestion and pressure
nasal congestion
temporarily reduces fever
promotes nasal and/or sinus drainage

Warnings
Liver warning: This product contains acetaminophen. Severe liver damage may occur if your child takes: more than 5 doses in 24 hours, which the maximum daily amount for this product
with other drugs containing acetaminophen

Do not use
with any other drug containing acetaminophen (prescription or nonprescription). If you are not sure whether a drug contains acetaminophen, ask a doctor or pharmacist.
in a child who is taking a prescription monoamine oxidase inhibitor (MAOI) (certain drugs for depression, psychiatric or emotional conditions, or Parkinson’s disease). If you do not know whether a prescription drug contains an MAOI, ask a doctor or pharmacist.
for 2 weeks after stopping the MAOI drug

Ask a doctor before use if the user has
liver disease
heart disease
high blood pressure
thyroid disease
diabetes
glaucoma
a breathing problem such as chronic bronchitis

Ask a doctor or pharmacist before use if the user is
taking the blood thinning drug warfarin
taking sedatives or tranquilizers
taking a prescription drug and you do not know if it contains an MAOI

When using this product
do not exceed recommended dosage
may cause drowsiness (sedatives and tranquilizers may increase the drowsiness effect)
may cause excitability especially in children

Stop use and ask a doctor if
sore throat persists for more than 2 days
sore throat is severe
sore throat is accompanied or followed by: fever, headache, rash, nausea, vomitting
pain or nasal congestion gets worse or lasts more than 5 day
fever gets worse or lasts more than 3 days
redness or swelling is presen
new symptoms occur
if nervousness, dizziness, or sleeplessness occur

PREGNANCY OR BREAST FEEDING

If pregnant or breast-feeding, ask a health professional before use.

KEEP OUT OF REACH OF CHILDREN

Do not give to children under 6 years of age unless directed by a doctor.

Keep out of reach of children. In case of overdose, get medical help or contact a Poison Control Center right away. Prompt medical attention is critical for adults as well as children even if you do not notice any signs or symptoms.

Directions
children 6 to under 12 years of age: Chew tablet before swallowing. 4 tablets every 4 hours while symptoms persist, not to exceed 5 doses (20 tablets) in 24 hours, or as directed by a doctor
children under 6 of age : consult a doctor

Other information
Phenylketonurics: contains Phenylalanine 4.2mg per tablet
protect from light
store between 15 to 30 C (59 to 86 F)
keep in a dry place

Inactive ingredients
Aspartame, citric acid, corn starch, FDC yellow no. 6 aluminum lake, magnesium stearate, mannitol, pineapple flavor, povidone K30

Questions or comments? (888) 221-3496 M-F 9 am to 5 pm
you may also use this number to report serious adverse events associated with the use of this product

PACKAGE LABEL

Children's Coltalin

NDC 51467-006-01

Acetaminophen - Pain Reliever-Fever Reducer
Chlorpheniramine maleate - Antihistamine
Phenylephrine hydrochloride- Decongestant

See new warnings information

Sugar Free

Aspirin Free

24 Chewable Tablets

Safety Sealed
Do not use if individually sealed foil unit dose pouches are torn, broken, or shows the evidence of being opened.